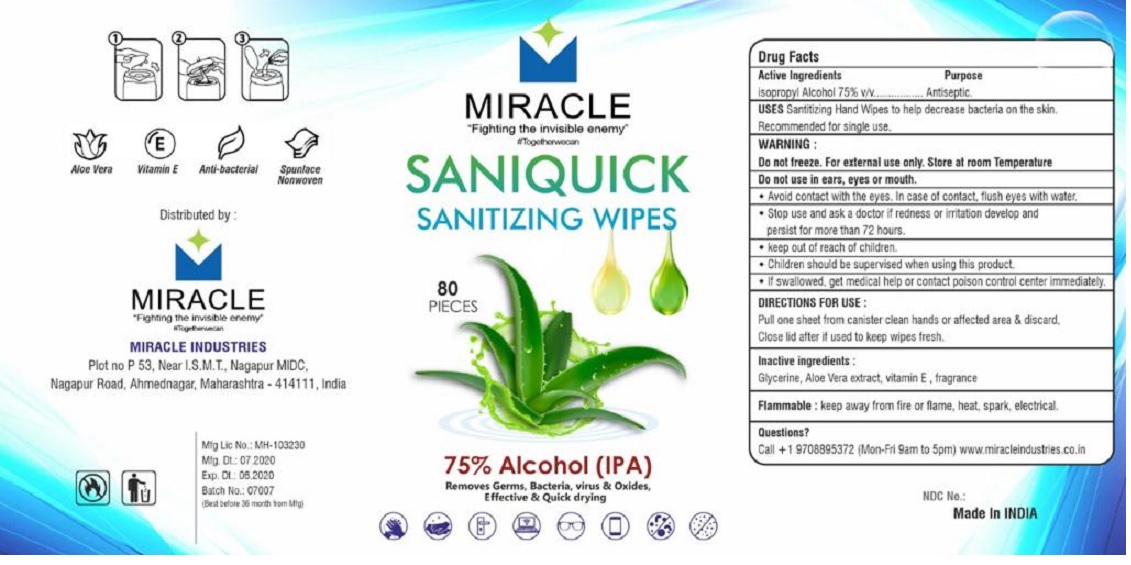 DRUG LABEL: MIRACLE SANIQUICK SANITIZING WIPES
NDC: 81257-101 | Form: CLOTH
Manufacturer: Miracle Industries
Category: otc | Type: HUMAN OTC DRUG LABEL
Date: 20210108

ACTIVE INGREDIENTS: ISOPROPYL ALCOHOL 75 mL/100 mL
INACTIVE INGREDIENTS: GLYCERIN; ALOE VERA LEAF; .ALPHA.-TOCOPHEROL

MIRACLE SANIQUICK SANITIZING WIPES

Active Ingredients

Isopropyl Alcohol 75% v/v

Purpose

Antiseptic.

USES

Sanitizing Hand Wipes to help decrease bacteria on the skin.

Recommended for single use.

WARNING :

Do not freeze. Foe external use only. Store at room Temperature

Do not use in ears, eyes or mouth.

• Avoid contact with the eyes. In case of contact, flush eyes with water.

• Stop use and ask a doctor if redness or irritation develop and persist for more than 72 hours.

Flammable : keep away from fire or flame, heat, spark, electrical

• keep out of reach of children.

• Children should be supervised when using this product.

• If swallowed, get medical help or contact a poison control center immediately.

DIRECTIONS FOR USE :

Pull one sheet from canister clean hands or affected area & discard,

Close lid after if used to keep wipes fresh.

Inactive ingredients :

Glycerine, Aloe Vera extract, vitamin E, fragrance

Questions?

Call +1 9708895372 (Mon-Fri 9am to 5pm) www.miracleindustries.co.in

*Fighting the invisible enemy*

#Togetherwecan

75% Alcohol (IPA)

Removes Germs, Bacteria, virus & Oxides, Effective & Quick drying

Aloe Vera

Vitamin E

Anti-bacterial

Spunlace Nonwoven

Distributed by :

MIRACLE INDUSTRIES

Plot no P 53, Near I.S.M.T., Nagapur MIDC,

Nagapur Road, Ahmednagar, Maharashtra - 414111, India

Made in INDIA